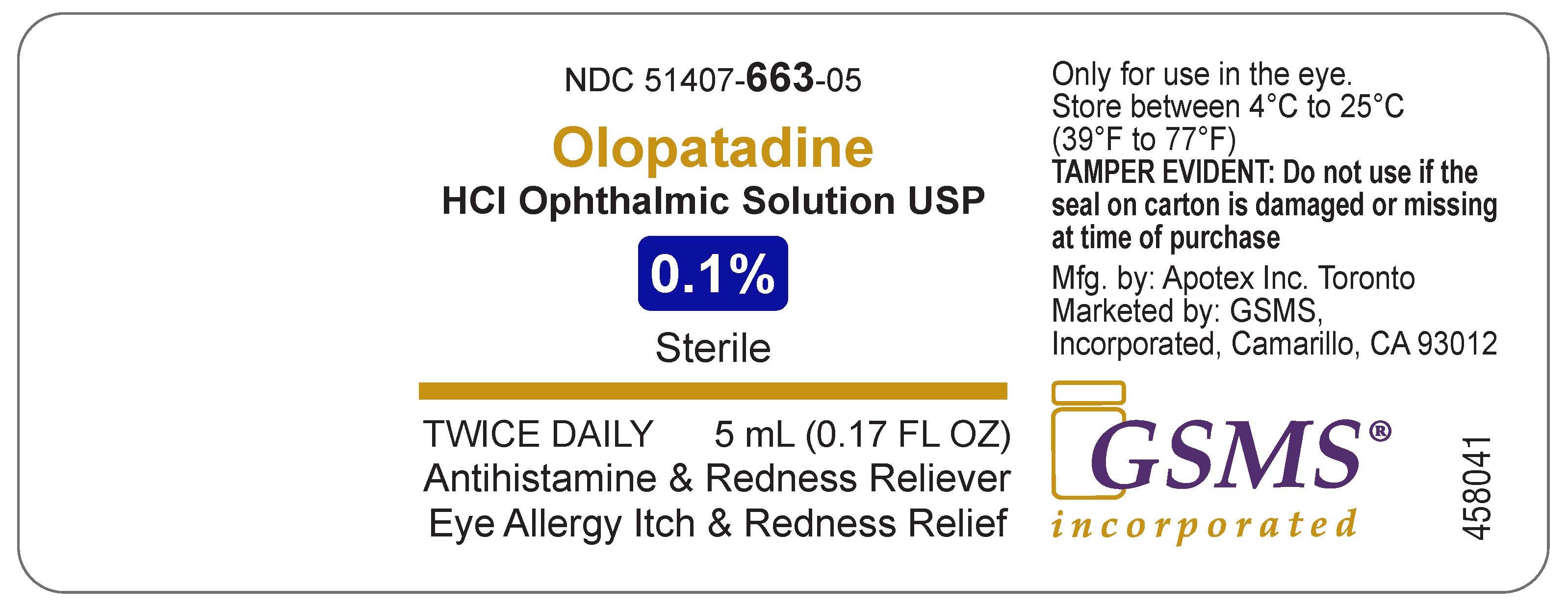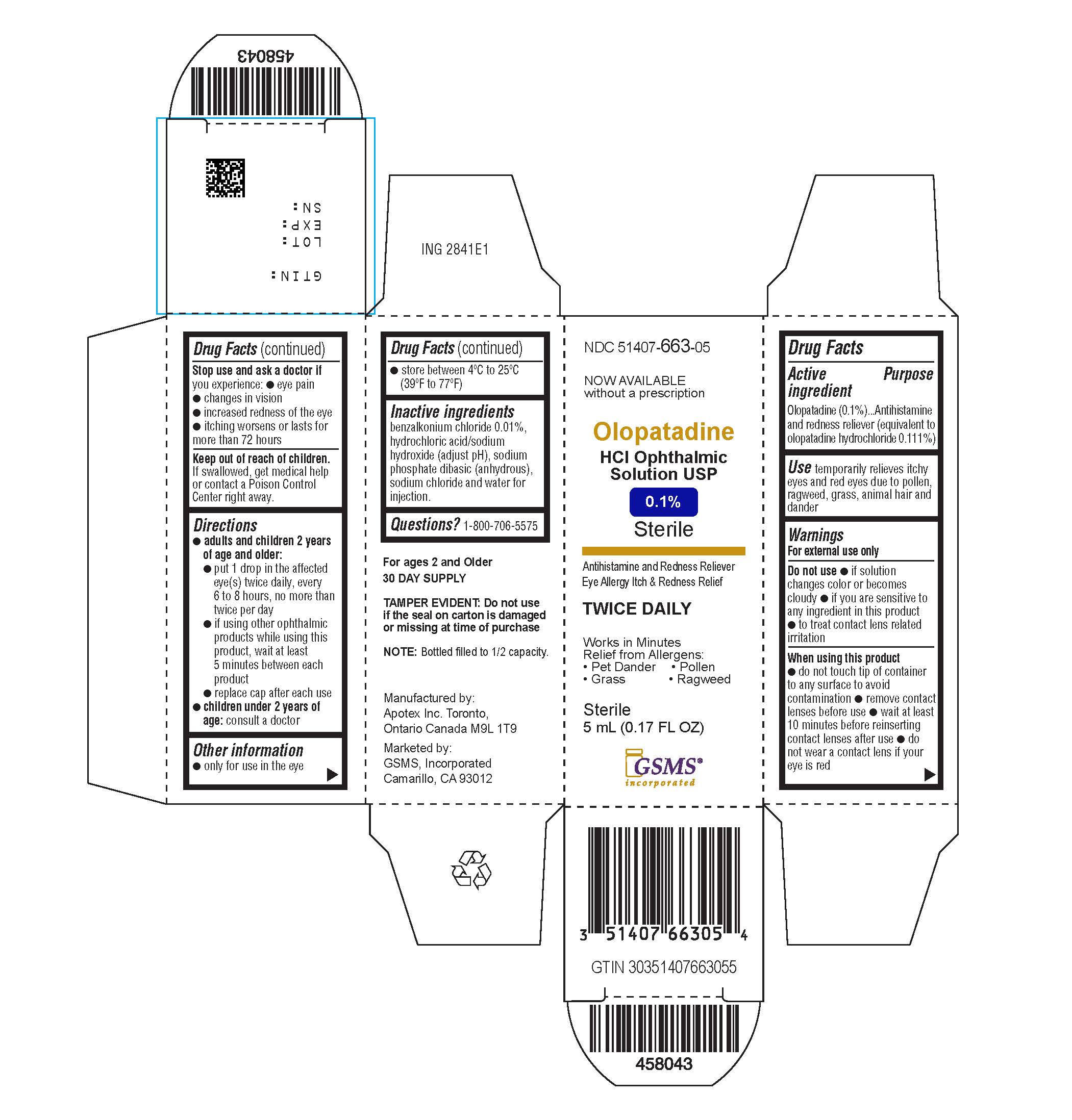 DRUG LABEL: Olopatadine hydrochloride
NDC: 51407-663 | Form: SOLUTION/ DROPS
Manufacturer: Golden State Medical Supply, Inc.
Category: otc | Type: HUMAN OTC DRUG LABEL
Date: 20251124

ACTIVE INGREDIENTS: OLOPATADINE HYDROCHLORIDE 1 mg/1 mL
INACTIVE INGREDIENTS: SODIUM PHOSPHATE, DIBASIC, ANHYDROUS; SODIUM CHLORIDE; HYDROCHLORIC ACID; SODIUM HYDROXIDE; WATER; BENZALKONIUM CHLORIDE

OLOPATADINE HYDROCHLORIDE solution/ drops.

Active ingredient (in each tablet)

Olopatadine (01.%) (equivalent to olopatadine hydrochloride 0.111%)

Purpose

Antihistamine and redness reliever

Uses

Temporarily relieves itchy and red eyes due to pollen, ragweed, grass, animal hair and dander.

Warnings

For external use only

Do not use

- If solution changes color or becomes cloudy
- If you are sensitive to any ingredient in this product
- To treat contact lens related irritation

When using this product

- Do not touch tip of container to any surface to avoid contamination
- Remove contact lenses before use
- Wait at least 10 minutes before reinserting contact lenses after use
- Do not wear a contact lens if your eye is red

Stop use and ask a doctor ifyou experience :

- Eye pain
- Changes in vision
- Increased redness of the eye
- Itching worsens or lasts for more than 72 hours

Keep out of reach of children.

If swallowed, get medical help or contact a Poison Control Center right away.

Directions

- adults and children 2 years and older:
  - put 1 drop in the affected eye(s) twice daily, every 6 to 8 hours, no more than twice per day
  - if using other ophthalmic products while using this product, wait at least 5 minutes between each product
  - replace cap after each use
- children under 2 years of age:

Consult a doctor

Other information

- Only for use in the eye
- Store between 4ºC to 25ºC (39ºF to 77ºF)

Inactive ingredients

benzalkonium chloride 0.01%, dibasic sodium phosphate (anhydrous), hydrochloric acid and/or sodium hydroxide (to adjust pH), purified water and sodium chloride

Questions?

1-800-706-5575

Marketed by:
GSMS, Inc.
Camarillo, CA 93012 USA

Principal Display Panel

TWICE DAILY RELIEF

Olopatadine HCl Ophthalmic Solution, USP 0.1%

Antihistamine and Redness Reliever

Eye Allergy Itch & Redness Relief

NDC 51407-663-05